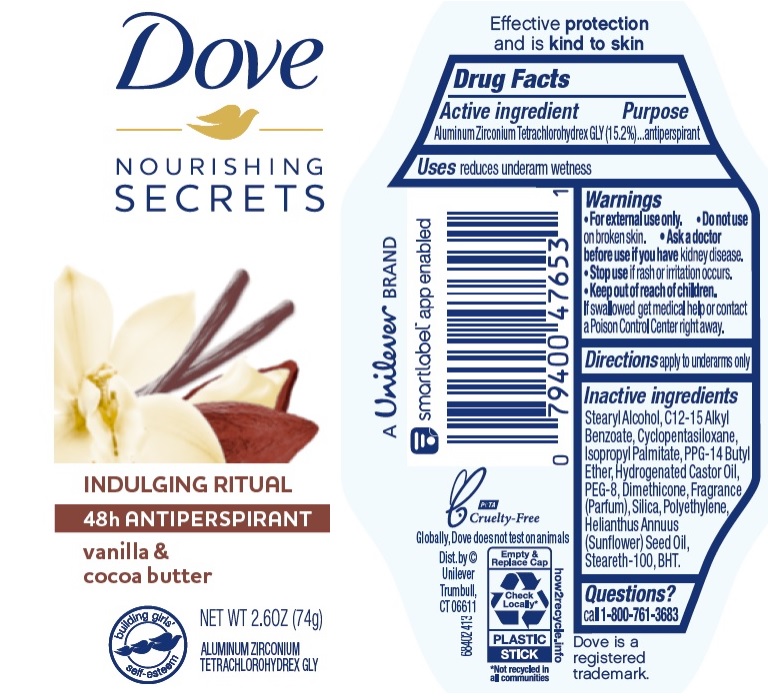 DRUG LABEL: Dove
NDC: 64942-1750 | Form: STICK
Manufacturer: Conopco Inc. d/b/a/ Unilever
Category: otc | Type: HUMAN OTC DRUG LABEL
Date: 20241110

ACTIVE INGREDIENTS: ALUMINUM ZIRCONIUM TETRACHLOROHYDREX GLY 15.2 g/100 g
INACTIVE INGREDIENTS: HIGH DENSITY POLYETHYLENE; CYCLOMETHICONE 5; HYDROGENATED CASTOR OIL; BUTYLATED HYDROXYTOLUENE; PPG-14 BUTYL ETHER; STEARYL ALCOHOL; SUNFLOWER OIL; SILICON DIOXIDE; ALKYL (C12-15) BENZOATE; DIMETHICONE; STEARETH-100; POLYETHYLENE GLYCOL 400; ISOPROPYL PALMITATE

Dove Nourishing Secrets Indulging Ritual Vanilla & Cocoa Butter 48h Antiperspirant

DOVE NOURISHING SECRETS INDULGING RITUAL VANILLA & COCOA BUTTER 48H ANTIPERSPIRANT - aluminum zirconium tetrachlorohydrex gly stick

Dove Nourishing Secrets Indulging Ritual Vanilla & Cocoa Butter 48h Antiperspirant

Drug Facts

Active ingredient

Aluminum Zirconium Tetrachlorohydrex GLY (15.2 %)

Purpose

antiperspirant

Uses

reduces underarm wetness

Warnings

• For external use only.
• Do not use on broken skin .
• Ask a doctor before use if you have kidney disease.
• Stop use if rash or irritation occurs.

• Keep out of reach of children.

If swallowed, get medical help or contact a Poison Control Center right away.

Directions

apply to underarms only

Inactive ingredients

Stearyl Alcohol, C12-15 Alkyl Benzoate, Cyclopentasiloxane, Isopropyl Palmitate, PPG-14 Butyl Ether, Hydrogenated Castor Oil, PEG-8, Dimethicone, Fragrance (Parfum), Silica, Polyethylene, Helianthus Annuus (Sunflower) Seed Oil, Steareth-100, BHT.

Questions?

Call toll-free 1-800-761-3683